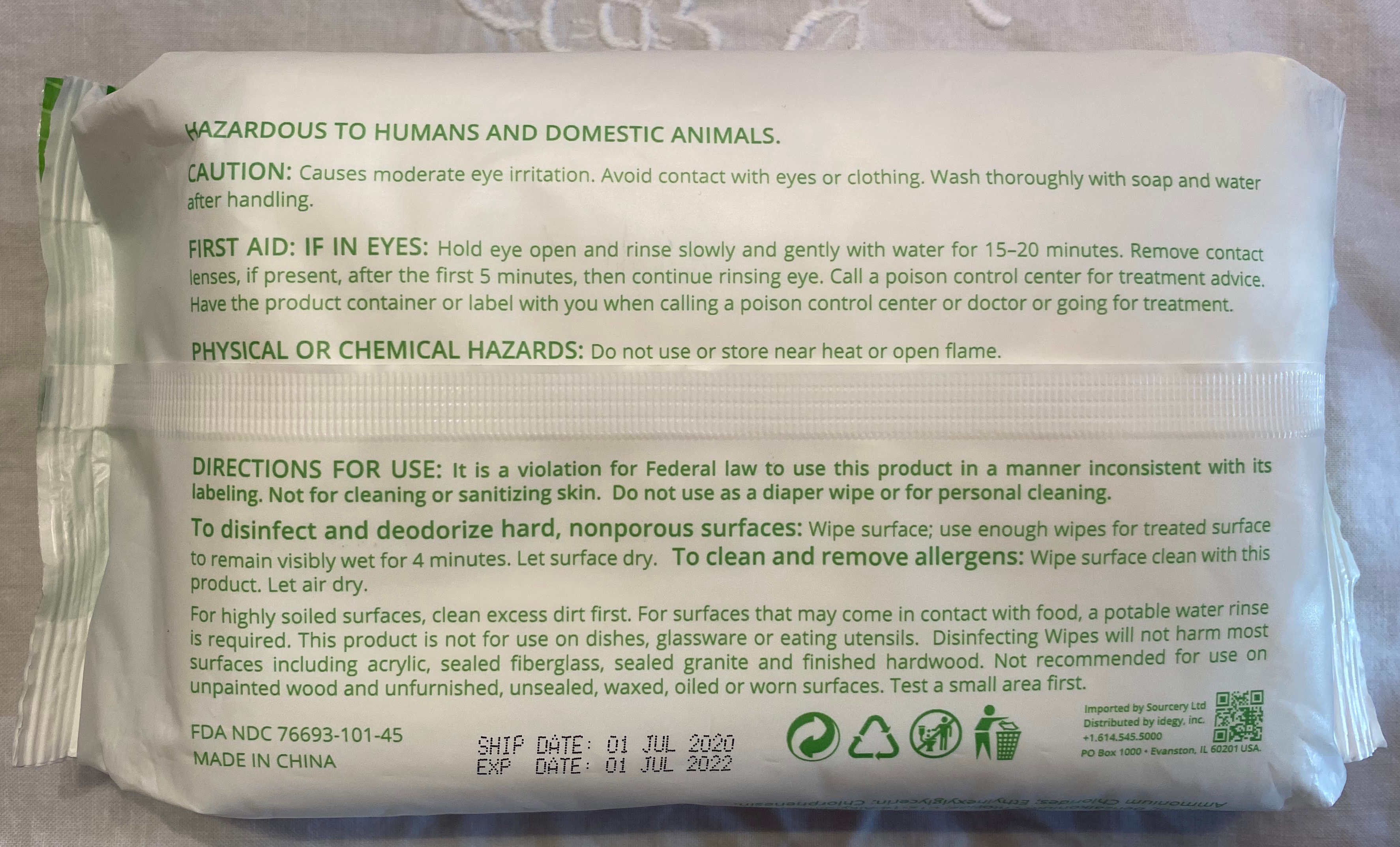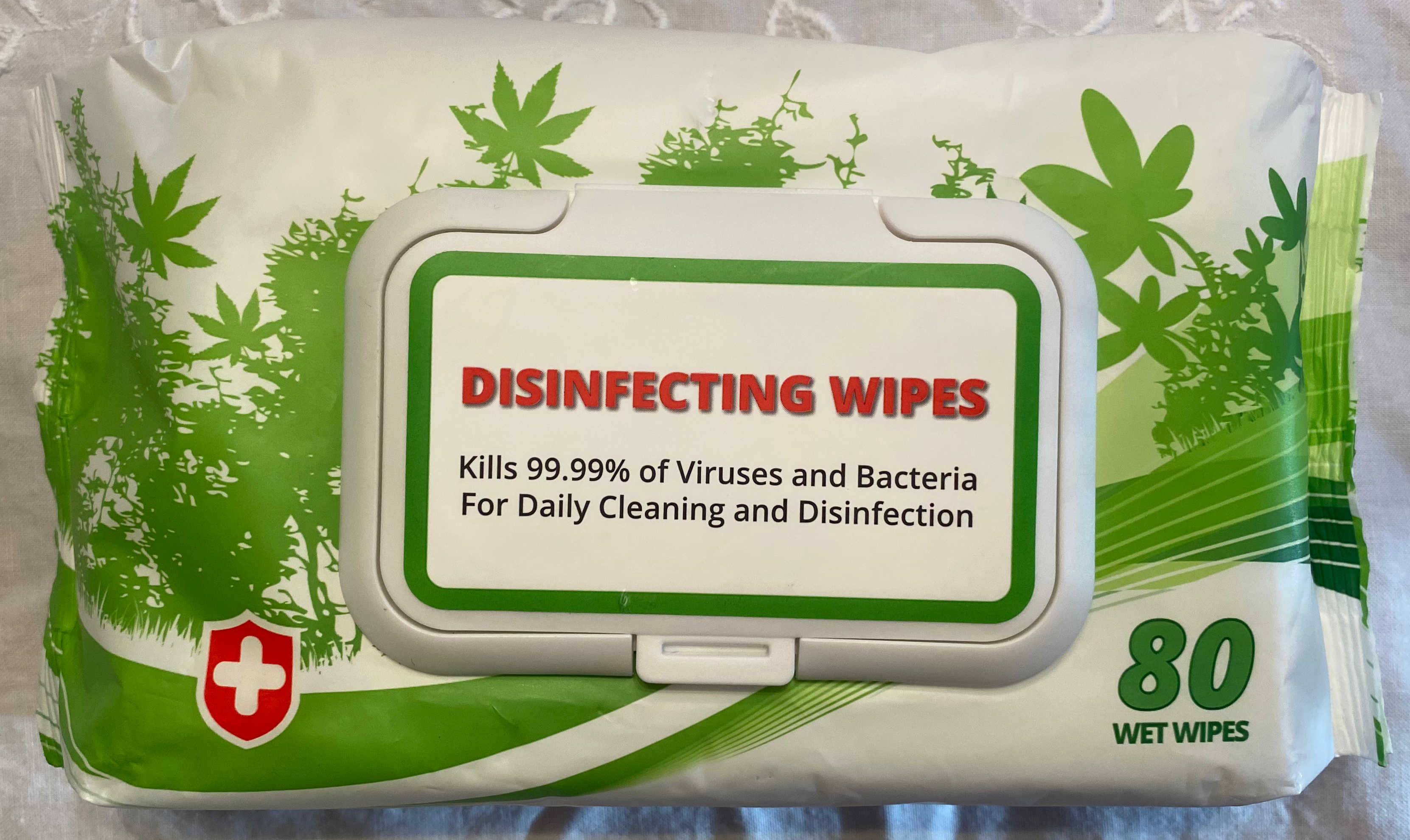 DRUG LABEL: Wet Wipes
NDC: 76693-101 | Form: CLOTH
Manufacturer: Sourcery Ltd
Category: otc | Type: HUMAN OTC DRUG LABEL
Date: 20200531

ACTIVE INGREDIENTS: BENZALKONIUM 0.06 g/100 g; PHENOXYETHANOL 0.3 g/100 g; DIDECYLDIMONIUM CHLORIDE 0.4 g/100 g; CHLORPHENESIN 0.1 g/100 g; ALCOHOL 10 g/100 g
INACTIVE INGREDIENTS: GLYCERIN 0.1 g/100 g; WATER 48.97 g/100 g; FRAGRANCE LAVENDER & CHIA F-153480 0.02 g/100 g

Alcohol-Based Wet Wipe

Active Ingredient(s)

Alcohol, Benzalkonium Chloride, C12-14-Alkyldimethyl(Ethylbenzyl) Ammonium Chlorides, Ethylhexylglycerin, Chlorphenesin

Purpose

Antiseptic, disinfection and surface cleaning

Use

TO disinfect and deodorize hard, nonporous surfaces.

Do not use or store near heat or open flame.

When using this product keep out of eyes, ears, and mouth. In case of contact with eyes, rinse eyes thoroughly with water.
Stop use and ask a doctor if irritation or rash occurs. These may be signs of a serious condition.
Keep out of reach of children. If swallowed, get medical help or contact a Poison Control Center right away.

Stop use and ask a doctor if irritation or rash occurs. These may be signs of a serious condition.

Keep out of reach of children. If swallowed, get medical help or contact a Poison Control Center right away.

Other information

- Store between 15-30C (59-86F)
- Avoid freezing and excessive heat above 40C (104F)
- Do not use or store near open heat or flame.

Inactive ingredients

glycerin, purified water, fragrance

PACKAGE LABEL

Package Label - Principal Display Panel

80 wipes

NDC 7663-101-45